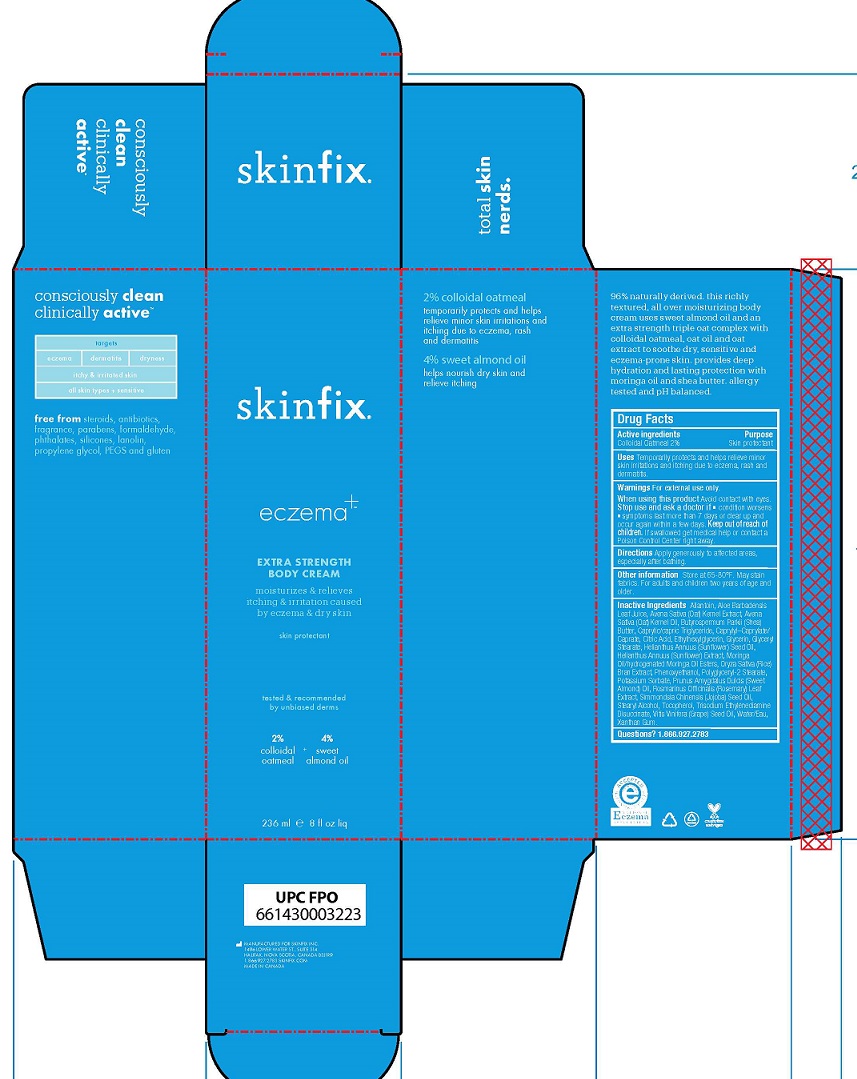 DRUG LABEL: EXTRA STRENGTH BODY
NDC: 54291-038 | Form: CREAM
Manufacturer: Canadian Custom Packaging Company
Category: otc | Type: HUMAN OTC DRUG LABEL
Date: 20241210

ACTIVE INGREDIENTS: OATMEAL 2 g/100 mL
INACTIVE INGREDIENTS: ALLANTOIN; ALOE VERA LEAF; AVENA SATIVA WHOLE; OAT KERNEL OIL; SHEA BUTTER; MEDIUM-CHAIN TRIGLYCERIDES; CAPRYLYL CAPRYLATE/CAPRATE; ANHYDROUS CITRIC ACID; ETHYLHEXYLGLYCERIN; GLYCERIN; GLYCERYL MONOSTEARATE; SUNFLOWER OIL; HELIANTHUS ANNUUS WHOLE; MORINGA OLEIFERA SEED OIL; RICE BRAN; PHENOXYETHANOL; POLYGLYCERYL-2 STEARATE; POTASSIUM SORBATE; ALMOND OIL; ROSEMARY; JOJOBA OIL; STEARYL ALCOHOL; TOCOPHEROL; TRISODIUM ETHYLENEDIAMINE DISUCCINATE; GRAPE SEED OIL; WATER; XANTHAN GUM

Extra Strength Body Cream

Active Ingredients

Colloidal Oatmeal 2%

Purpose

Skin protectant

Uses

Temporarily protects and helps relieve minor skin irritations and itching due to eczema rash and dermatitis.

Warnings

For external use only.

When using this product, avoid contact with eyes.

Stop use and ask a doctor if

- condition worsens
- symptoms last more than 7 days or clear up and occur again within a few days.

When using this product

- Avoid contact with eyes

Stop use and ask a doctor if

- condition worsens
- symptoms last more than 7 days or clear up and occur again within a few days

Keep out of reach of children. If swallowed get medical help or contact a Poison Control Center right away.

Directions

Apply generously to affected areas, especially after bathing.

Inactive Ingredients

allantoin, aloe barbadensis leaf juice, avena sativa (oat) extract, avena sativa kernel oil, butyrospermum parkii (shea) butter, caprylic/capric triglyceride, caprylyl–caprylate/caprate citric acid, ethylhexylglycerin, glycerin, glyceryl stearate, helianthus annuus (sunflower) seed oil, helianthus annuus (sunflower) extract, moringa oil/hydrogenated moringa oil esters, oryza sativa (rice) bran extract, phenoxyethanol, polyglyceryl-2-stearate, potassium sorbate, rosmarinus officinalis (rosemary) leaf extract, simmondsia chinensis (jojoba) seed oil, stearyl alcohol, tocopherol, trisodium ethylenediamine disuccinate, vitis vinifera (grape) seed oil, water/aqua, xanthan gum.